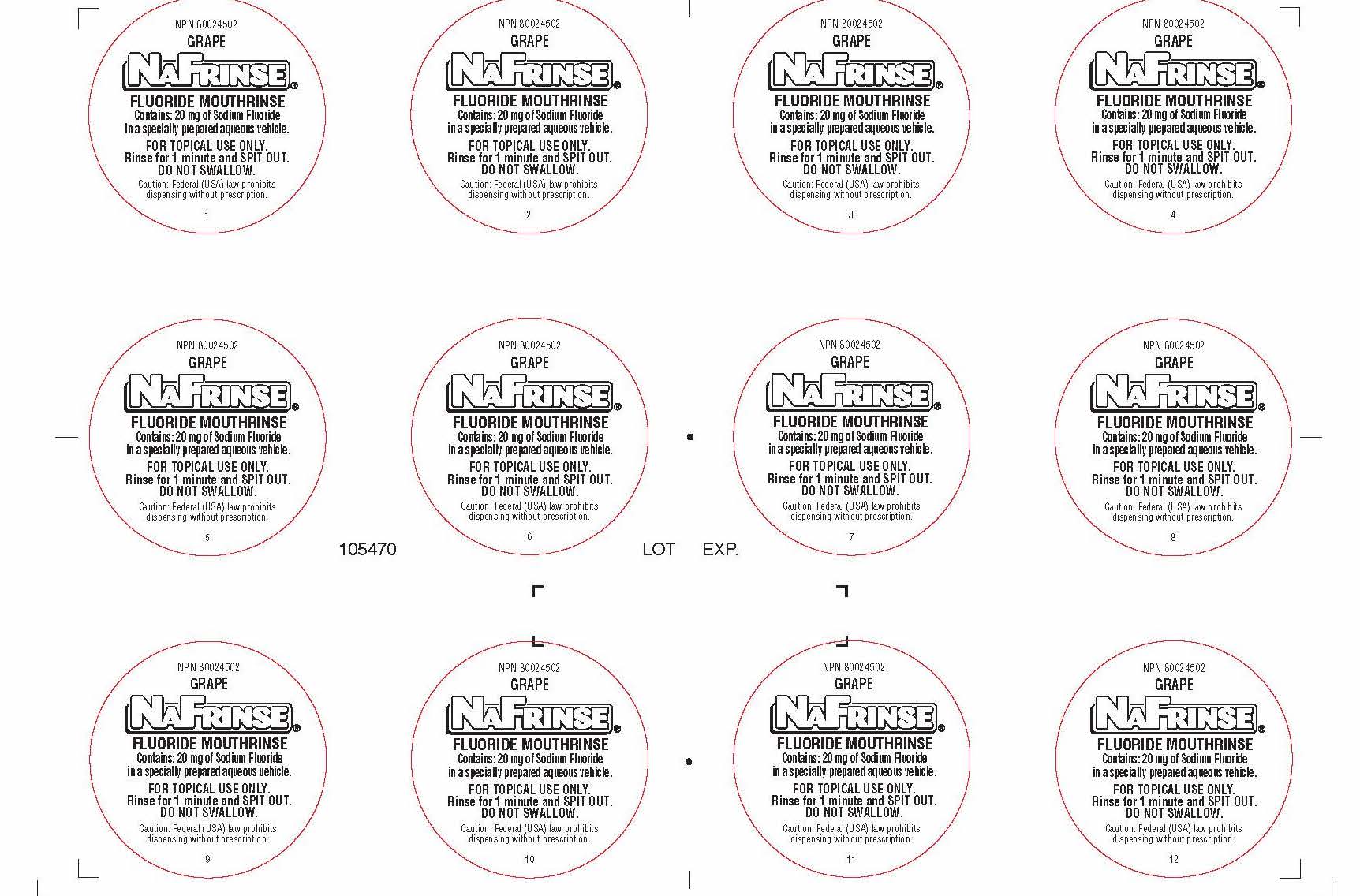 DRUG LABEL: NAFRINSE UNIT DOSE FLUORIDE
NDC: 0273-8001 | Form: SOLUTION
Manufacturer: Young Dental Manufacturing Co 1, LLC.
Category: prescription | Type: HUMAN PRESCRIPTION DRUG LABEL
Date: 20181214

ACTIVE INGREDIENTS: Sodium Fluoride 20 mg/10 mL
INACTIVE INGREDIENTS: SACCHARIN SODIUM; Potassium Sorbate; ANHYDROUS CITRIC ACID

Inactives

Saccharin Sodium, Potassium Sorbate, Citric Acid, Flavoring

Dye

Warning:

For Topical use only.

Federal (USA) law prohibits dispensing without prescription

Directions

Rinse for 1 minute and spit out. Do not swallow.